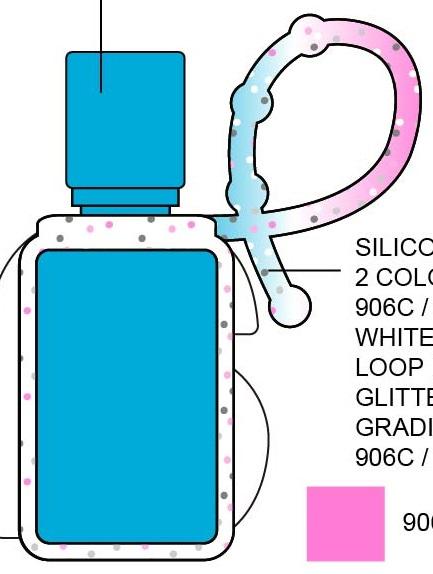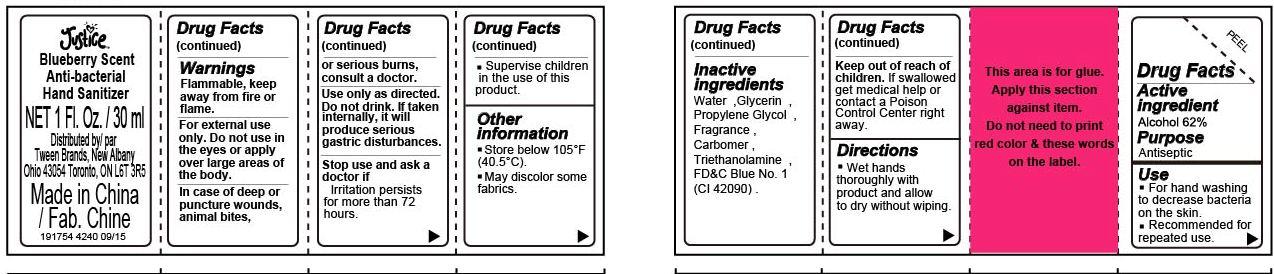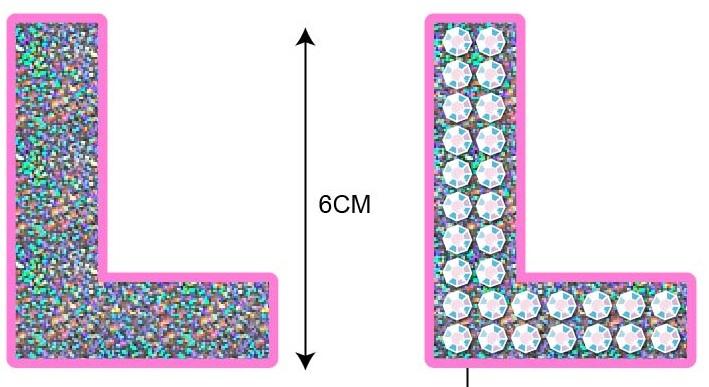 DRUG LABEL: Justice Letter L Blueberry Scent Anti-bacterial Hand Sanitizer
NDC: 60637-043 | Form: GEL
Manufacturer: Tween Brands, Inc.
Category: otc | Type: HUMAN OTC DRUG LABEL
Date: 20221007

ACTIVE INGREDIENTS: ALCOHOL 620 mg/1 mL
INACTIVE INGREDIENTS: WATER; GLYCERIN; PROPYLENE GLYCOL; TROLAMINE; FD&C BLUE NO. 1

Justice Letter L Blueberry Scent Anti-bacterial Hand Sanitizer

Active Ingredient

Alcohol 62%

Purpose

Antiseptic

Use

- For hand washing to decrease bacteria on the skin.
- Recommended for repeated use.

Warnings

Flammable, keep away from fire or flame.

For external use only. Do not use in the eyes or apply over large areas of the body.

In case of deep or puncture wounds, animal bites, or serious burns, consult a doctor.

Use only as directed. Do not drink. If taken internally, it will produce serious gastric disturbances

Stop use and ask a doctor if

irritation persists for more than 72 hours.

Supervise children in the use of this product.

Other Information

- Store beow 105^0F (40.5^0C)
- May discolor some fabrics.

Keep out of reach of children.

If swallowed get medical help or contact a Poison Control Center right away.

Directions

- Wet hands thoroughly with product and allow to dry without wiping.

Inactive Ingredients

Water, Glycerin, Propylene Glycol, Fragrance, Carbomer, Triethanolamine, FD&C Blue No. 1 (CI 42090)